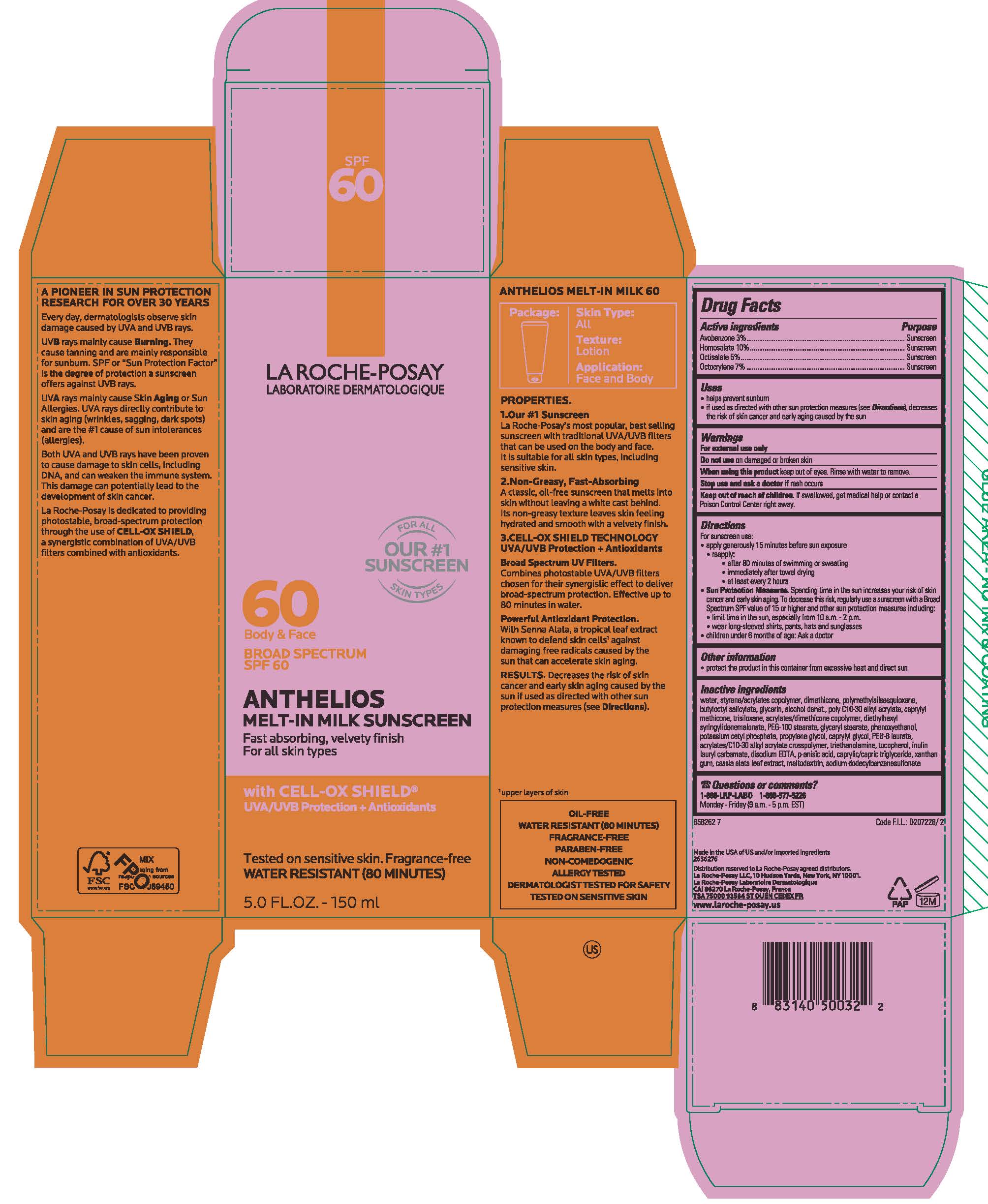 DRUG LABEL: La Roche Posay Face Body Anthelios SPF 60 Melt In Milk Fast absorbing, velvety finish for all skin types with Cell-OC Shield XL
NDC: 75897-105 | Form: LOTION
Manufacturer: Unette Corporation
Category: otc | Type: HUMAN OTC DRUG LABEL
Date: 20240229

ACTIVE INGREDIENTS: AVOBENZONE 30 mg/1 mL; HOMOSALATE 100 mg/1 mL; OCTISALATE 50 mg/1 mL; OCTOCRYLENE 70 mg/1 mL
INACTIVE INGREDIENTS: WATER; DIMETHICONE; BUTYLOCTYL SALICYLATE; GLYCERIN; ALCOHOL; CAPRYLYL TRISILOXANE; TRISILANE; DIETHYLHEXYL SYRINGYLIDENEMALONATE; PEG-100 STEARATE; GLYCERYL MONOSTEARATE; PHENOXYETHANOL; POTASSIUM CETYL PHOSPHATE; PROPYLENE GLYCOL; CAPRYLYL GLYCOL; PEG-8 LAURATE; TROLAMINE; TOCOPHEROL; EDETATE DISODIUM; P-ANISIC ACID; MEDIUM-CHAIN TRIGLYCERIDES; XANTHAN GUM; SENNA ALATA LEAF; MALTODEXTRIN

LRP AT 60 FACE AND BODY 1L SPF 60

Active ingredients

Avobenzone 3%

Homosalate 10%

Octisalate 5%

Octocrylene 7%

Purpose

Sunscreen

Uses

- helps prevent sunburn
- if used as directed with other sun protection measures (see Directions), decreases the risk of skin cancer and early skin aging caused by the sun

Warning

For external use only

Do not use

on damaged or broken skin

When using this product

keep out of eyes. Rinse with water to remove.

Stop use and ask a doctor if

rash occurs

Keep out of reach of children.

If swallowed, get medical help or contact a Poison Control Center right away.

Directions

For sunscreen use:
• apply generously 15 minutes before sun exposure
• reapply:
• after 80 minutes of swimming or sweating
• immediately after towel drying
• at least every 2 hours
• Sun Protection Measures. Spending time in the sun increases your risk of skin cancer and early skin aging. To decrease this risk, regularly use a sunscreen with a Broad Spectrum SPF value of 15 or higher and other sun protection measures including:
• limit time in the sun, especially from 10 a.m - 2 p.m.
• wear long-sleeved shirts, pants, hats and sunglasses
• children under 6 months of age: Ask a doctor

Other information

- protect the product in this container from excessive heat and direct sun

Inactive ingredients

water, sytrene/acrylates copolymer, dimethicone, polymethlysilsesquioxane, butylocytyl salicylate, glycerin, alcohol denat., poly C10-30 alkyl acrylate, caprylyl methicone, trisiloxane, acrylates/dimethicone copolymer, diethylhexyl syringylidenemalonate, PEG-100 stearate, glyceryl stearate, phenoxyethanol, potassium cetyl phosphate, propylene glycol, caprylyl glycol, PEG-8 laurate, acrylates/C10-30 alkyl acrylate crosspolymer, triethanolamine, tocopherol, inulin lauryl carbamate, disodium EDTA, p-anisic acid, caprylic/capric triglyceride, xanthan gum, cassia alata leaf extract, maltodextrin

Questions or comments?

1-888-LRP LABO 1-888-577-5226